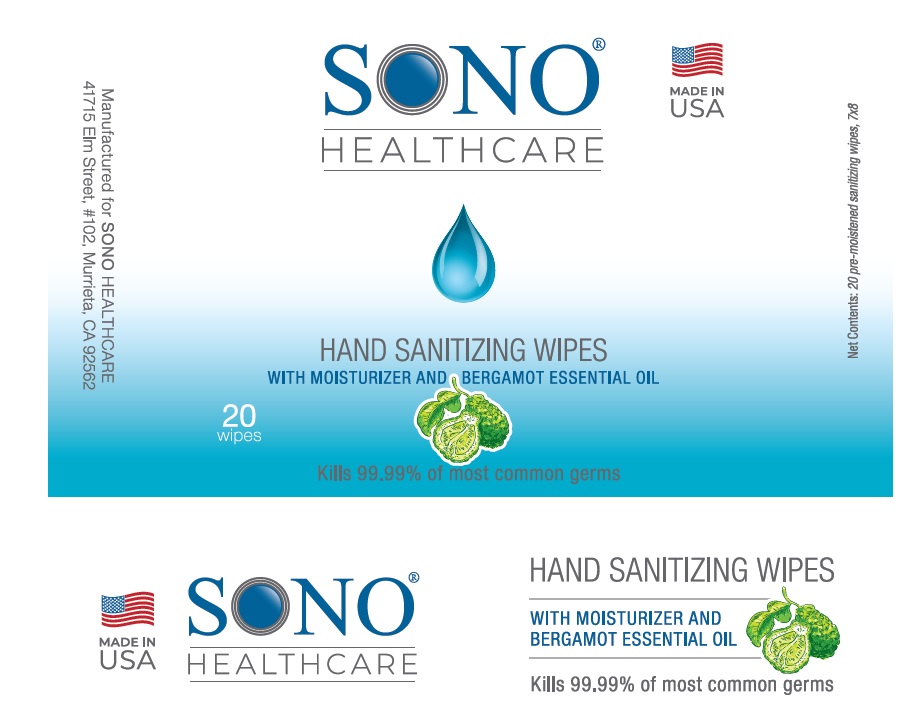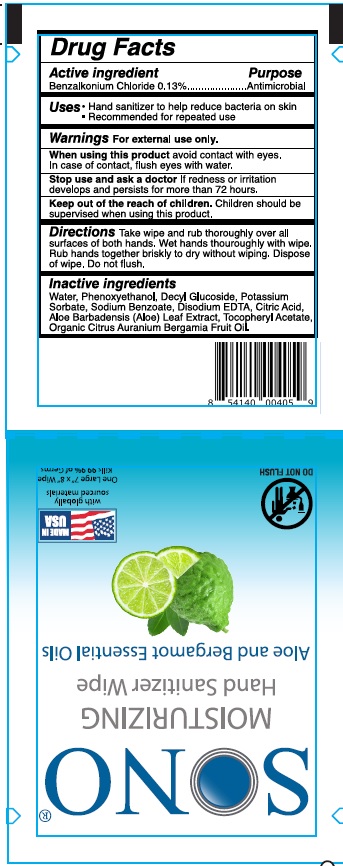 DRUG LABEL: Hand Wipes
NDC: 77677-013 | Form: SWAB
Manufacturer: Advanced Ultrasound Solutions Inc.
Category: otc | Type: HUMAN OTC DRUG LABEL
Date: 20251205

ACTIVE INGREDIENTS: BENZALKONIUM CHLORIDE 0.13 g/100 g
INACTIVE INGREDIENTS: PHENOXYETHANOL; WATER; DECYL GLUCOSIDE; POTASSIUM SORBATE; SODIUM BENZOATE; EDETATE DISODIUM ANHYDROUS; CITRIC ACID MONOHYDRATE; ALOE VERA LEAF; .ALPHA.-TOCOPHEROL ACETATE; BERGAMOT OIL

Drug Facts

Active ingredient

Benzalkonium chloride.........0.13%

Purpose

Antimicrobial

Uses

- For hand sanitizing to decrease bacteria on the skin
- Recommended for repeated use

Warnings

For external use only

Do not use if you are allergic to any of these ingredients

When using this product

Avoid contact with eyes. In case of eye contact, flush eyes with water.

Stop use and ask a doctor

If irritation or redness develops, or if condition persists for more than 72 hours.

Keep out of reach of children

If swallowed, get medical help or contact a Poison Control Center right away.

Directions

- adults and childrens 2 years and over: apply to hands, allow to dry without wiping
- children under 2 years: ask a doctor before use

To Dispense: Peel back front label slowly. Remove Wipes

To Reseal: Firmly rub thumb over label. Dispose of wipe in thrash. Do not flush

Other information

- Store below 95°F (35°C)
- keep closed tightly
- may discolor certain fabrics or surfaces

Inactive ingredients

Purified Water, Phenoxyethanol, Decyl Glucoside, Potassium Sorbate, Sodium Benzoate, Disodium EDTA, Citric Acid, Aloe Barbadensis (Aloe) Leaf Extract, Tocopheryl Acetate, Organic Citrus Auranium Bergamia Fruit Oil.

Principal Display Panel

NDC: 77677-013-20

SONO® HEALTHCARE

MADE IN USA

HAND SANITIZING WIPES

WITH MOISTURIZER AND BERGAMOT ESSENTIAL OIL

Kills 99.9% of most common germs

20 Wipes

New Contents: 20 pre-moistened sanitizing wipes, 7X8

NDC: 77677-013-01

SONO

HAND SANITIZING WIPES

Aloe and Bergamont Essental Oils

MADE IN USA

with globally sourced materials

One Large 7''x 8" Wipes

Kills 99.9% of Germs